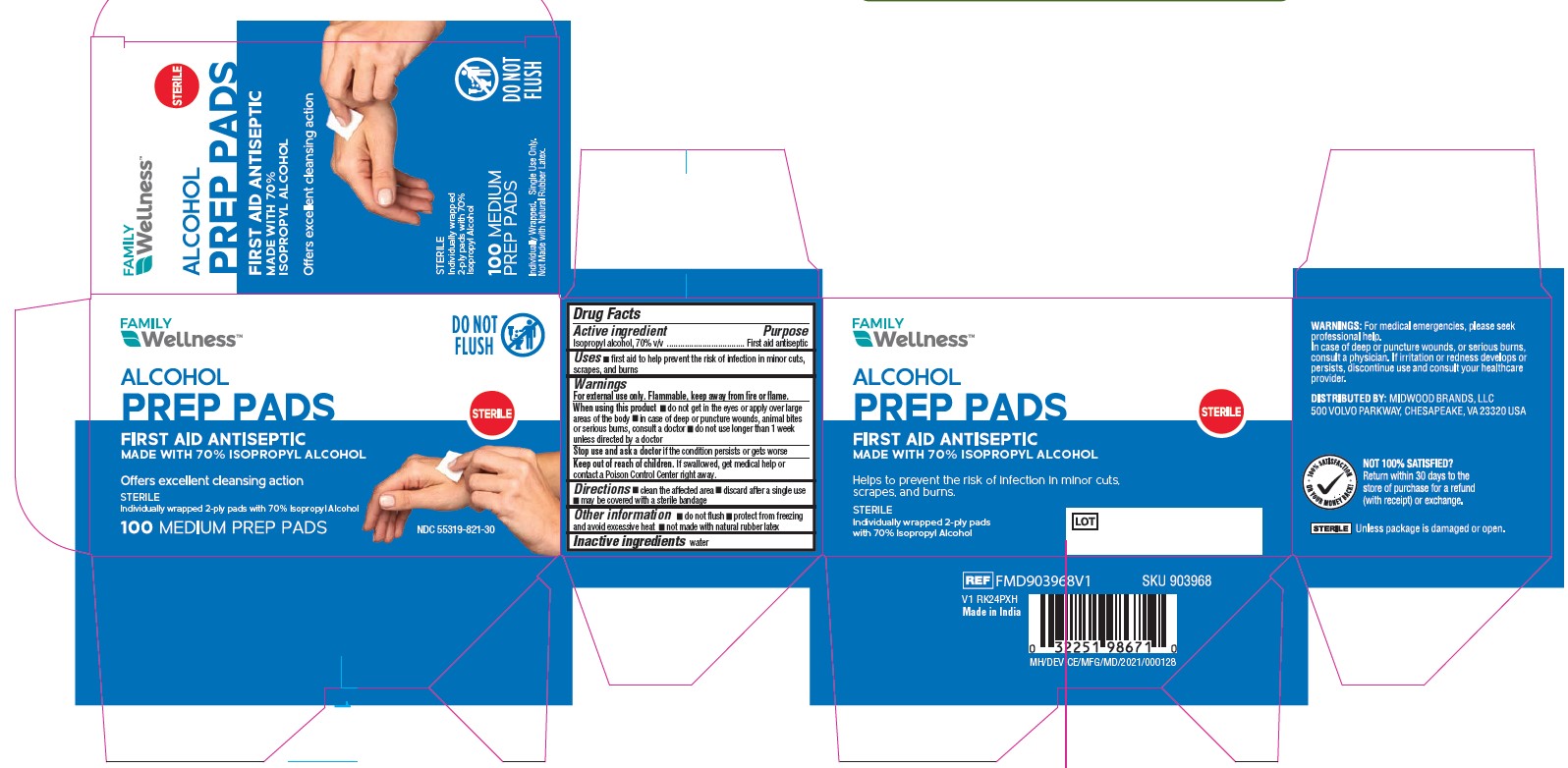 DRUG LABEL: Alcohol Prep Pads
NDC: 55319-821 | Form: SWAB
Manufacturer: Family Dollar Stores, Inc.
Category: otc | Type: HUMAN OTC DRUG LABEL
Date: 20250418

ACTIVE INGREDIENTS: ISOPROPYL ALCOHOL 70 mL/100 mL
INACTIVE INGREDIENTS: WATER

55319-821 Family Dollar IPA Prep Pad

Active Ingredient

Isopropyl alcohol, 70% v/v

Purpose

First aid antiseptic

Uses

- first aid to help prevent the risk of infection in minor cuts, scrapes, and burns

Warnings

For external use only. Flammable, keep away from fire or flame.

When using this product

- do not get in the eyes or apply over large areas of the body
- in case of deep or puncture wounds, animal bites or serious burns, consult a doctor
- do not use longer than 1 week unless directed by a doctor

Stop use and ask a doctor

if the condition persists or gets worse

Keep out of reach of children.

If swallowed, get medical help or contact a Poison Control Center right away.

Directions

- clean the affected area
- discard after a single use
- may be covered with a sterile bandage

Other information

- do not flush
- protect from freezing and avoid excessive heat
- not made with natural rubber latex

Inactive ingredients

water

Warnings:

For medical emergencies, please seek profesisonal help. In case of deep or puncture wounds, or serious burns, consult a physician. If irritation or redness develops or persists, discontinue use and consult your healthcare provider.

Manufacturing information

Distributed by: Midwood Brands, LLC

500 Volvo Parkway, Chesapeake, VA 23320 USA

Made in India

Ref: FMD903968V1

V1 RK24PHX